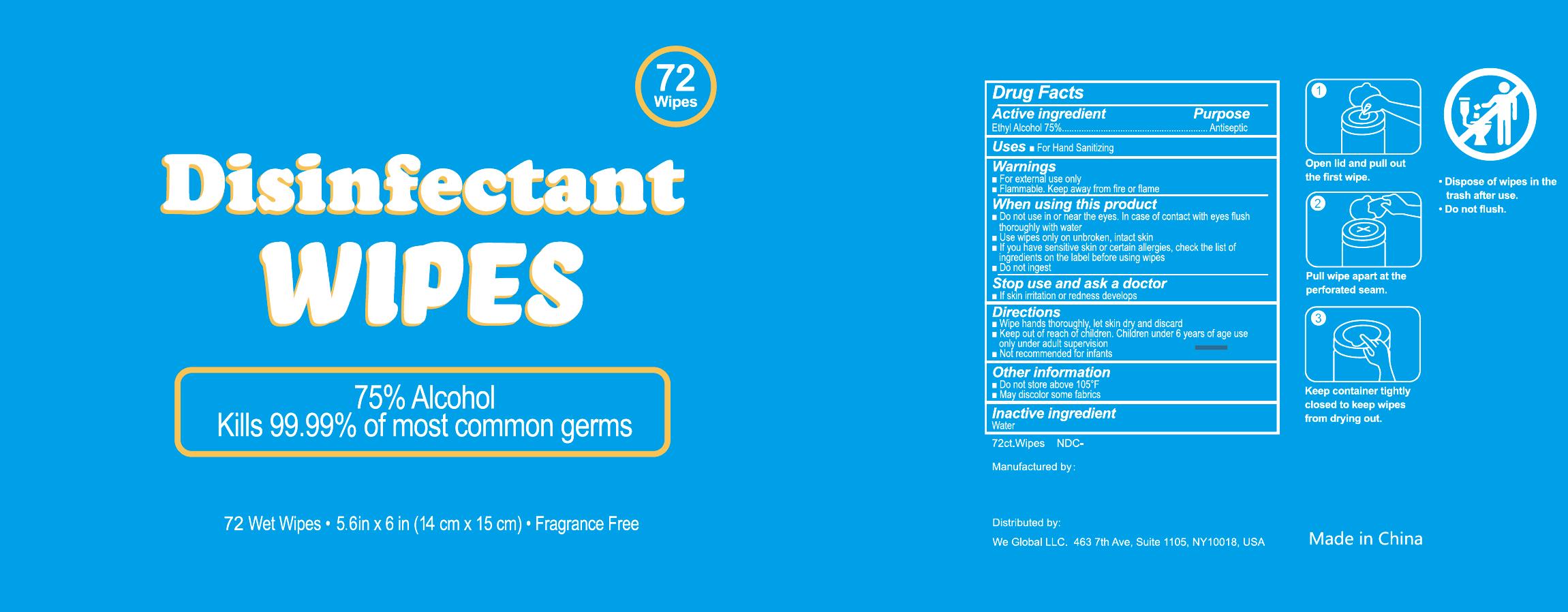 DRUG LABEL: Disinfectant Wipes
NDC: 78601-001 | Form: CLOTH
Manufacturer: Jiaxing Qinya Sanitary Products Co., Ltd.
Category: otc | Type: HUMAN OTC DRUG LABEL
Date: 20200920

ACTIVE INGREDIENTS: ALCOHOL 75 mL/100 mL
INACTIVE INGREDIENTS: WATER

78601-001 wet wipes 75% Ethyl Alcohol

ACTIVE INGREDIENT

Ethyl Alcohol 75%

PURPOSE

Antiseptic

USE

For Hand Sanitizing

Warning

■For external use only
■Flammable. Keep away from fire or flame
When using this product
DO not use in or near the eyes. In case of contact with eyes fush
thoroughly with water
. Use wipes only on unbroken, intact skin
”lfyou have sensitivev skin or Certain lerges check the list of
igredients on the label before using wipes
■Do not ingest

Stop use and ask a doctor
. If skin ritation or redness develops

KEEP OUT OF REACH OF CHILDREN

Keep out of rach o cildle Cildren under 6 years of age use
only under adult supervision
Not recommended for infants

Directions

. Wipe hands thoroughly, let skin dry and discard

Inactive ingredients

Water